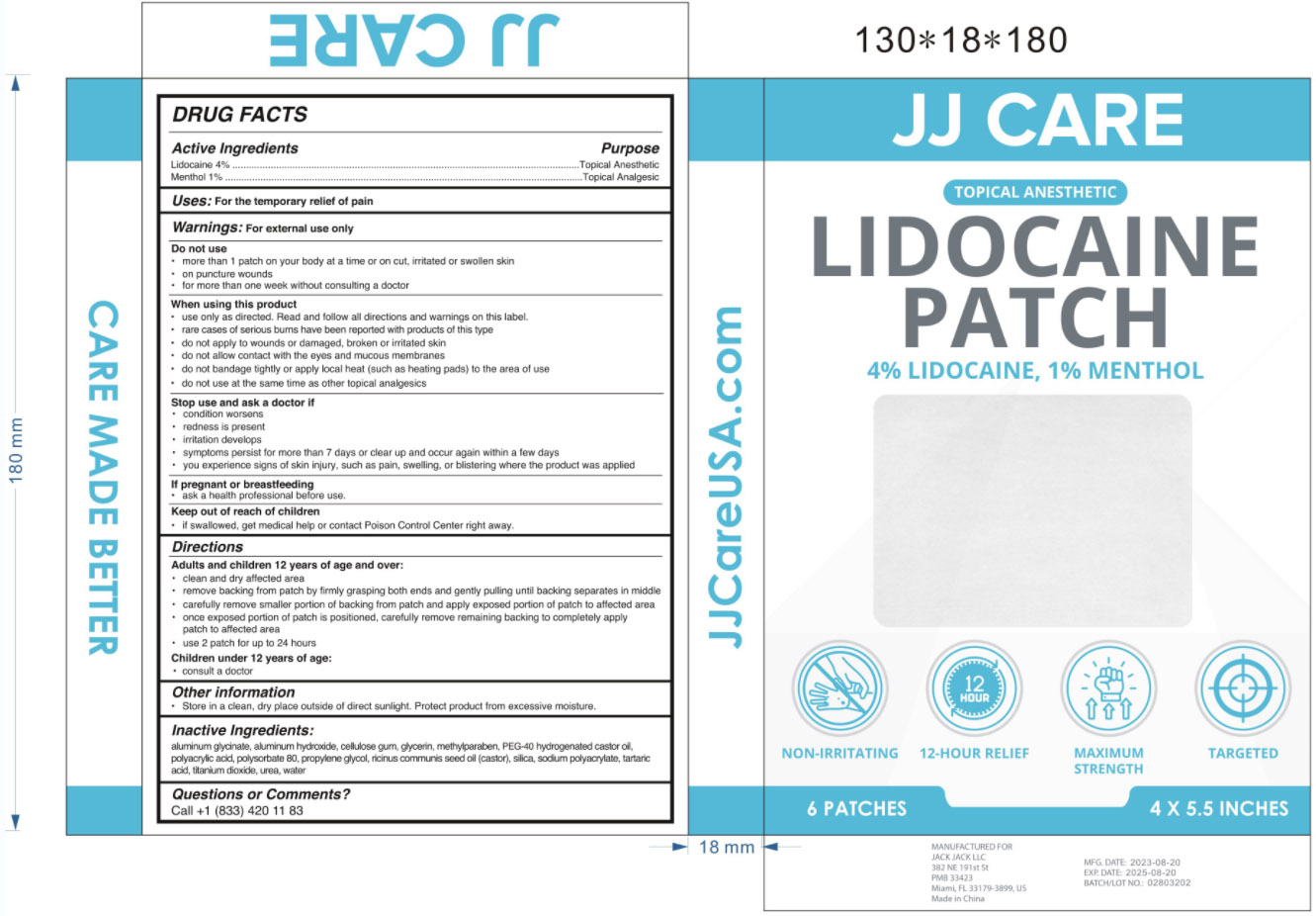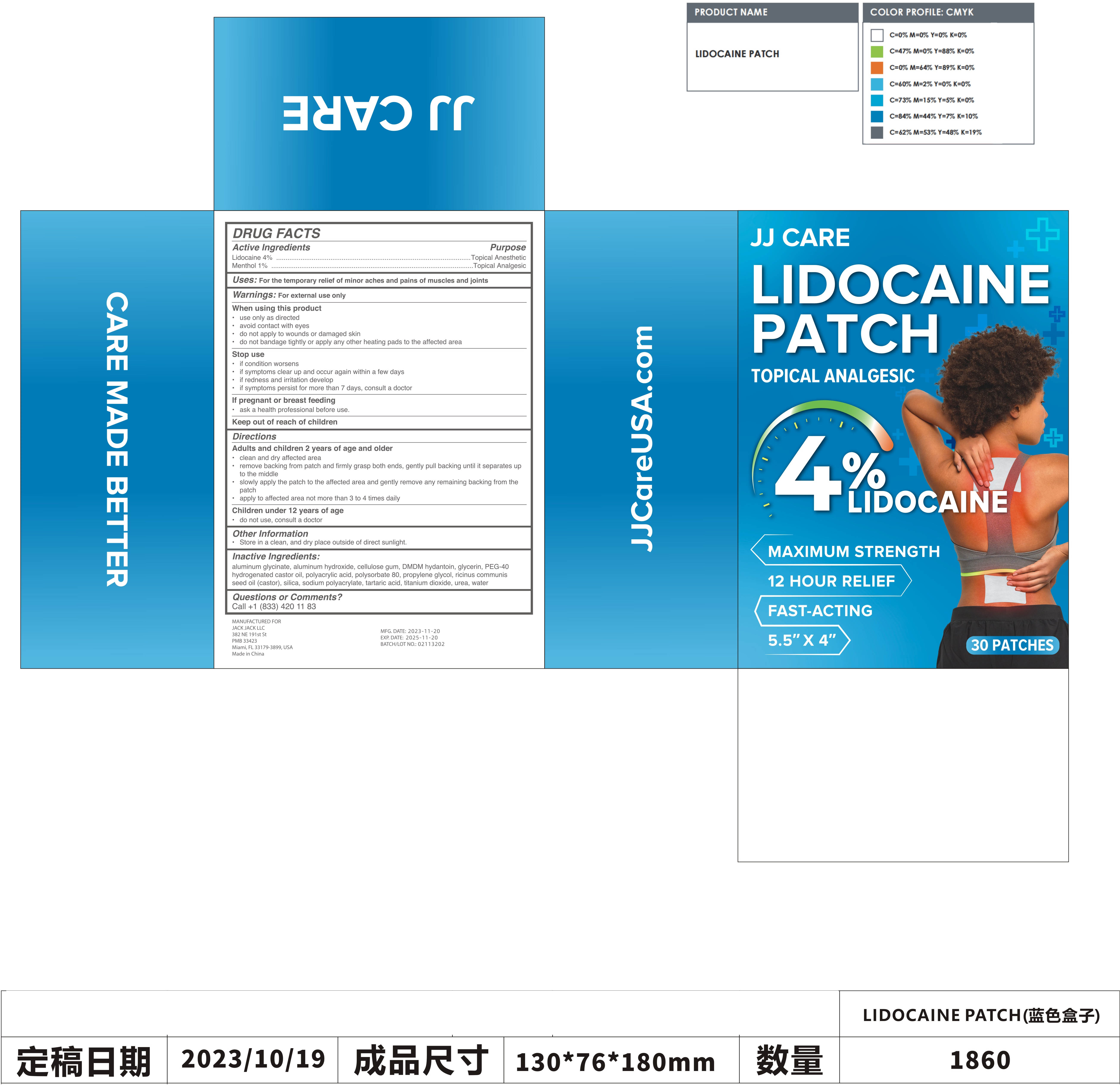 DRUG LABEL: Lidocaine Patch
NDC: 81484-901 | Form: PATCH
Manufacturer: Anhui Miao De Tang Pharmaceutical Co., Ltd.
Category: otc | Type: HUMAN OTC DRUG LABEL
Date: 20231114

ACTIVE INGREDIENTS: MENTHOL 0.01 g/1 1; LIDOCAINE 0.04 g/1 1
INACTIVE INGREDIENTS: POLYACRYLIC ACID (250000 MW); SODIUM POLYACRYLATE (2500000 MW); UREA; TARTARIC ACID; WATER; TITANIUM DIOXIDE; DIHYDROXYALUMINUM AMINOACETATE ANHYDROUS; CARBOXYMETHYLCELLULOSE; SILICON DIOXIDE; ALUMINUM HYDROXIDE; PROPYLENE GLYCOL; METHYLPARABEN; POLYSORBATE 80; CASTOR OIL; GLYCERIN; POLYOXYL 40 HYDROGENATED CASTOR OIL

Lidocaine Patch

Lidocaine Patch

ACTIVE INGREDIENT

Lidocaine 4%,Menthol 1%

PURPOSE

For the temporary relief of palin

INDICATIONS AND USAGE

For the temporary relief of palin, TOPICAL ANESTHETIC

WARNINGS

For external use only

DO NOT USE

more than 1 patch on your body at a time or on cut, irritated or swollen skin

WHEN USING

use only as directod. Read and follow all directions and warnings on this label.
rare cases of serious bums have been reported with products of this type
do not apply to wounds or damaged, broken or irritated skin
do not allow contact with the eyes and mucous membranes
do not bandage tightly or apply local heat (such as heating pads) to the area of use
do not use at the same time as other topical analgesics

STOP USE

condition worsens
rodness is present
irritation develops
symptoms persist for more than 7 days or clear up and occur again within a few days
you experience sians ot skin injury, such as pain, swelling, or blistering where the product was applied

KEEP OUT OF REACH OF CHILDREN

it swallowed, get medical help or contact Poison Control Center right away.

DOSAGE AND ADMINISTRATION

Adults and children 12 years of age and over:
clean and dry aftecied area
remove backing from patch by firmly grasping both ends and gently pulling until backing separates in middle
carefully remave smaller portion of backing from patch and apply exposed portion of patch to atlected area
once exposed portion of patch is positioned, carefully remove remaining backing to completely applypatch to aitected area
use 2 patch tor up to 24 hours
Children under 12 years of age:consult a doctor

STORAGE AND HANDLING

Store in a clean, dry place outside of direct sunlight. Protect product from excessive moisture.

INACTIVE INGREDIENT

Aluminum Glycinate
Aluminum Hydroxide
Cellulose Gum
Glycerin
Methylparaben
PEG-40 Hydrogenated Castor Oil
Polyacrylic Acid
Polysorbate 80
Propylene Glycol
Ricinus Communis Seed Oil (Castor)
Silica
Sodium Polyacrylate
Tartaric Acid
Titanium Dioxide
Urea
Water